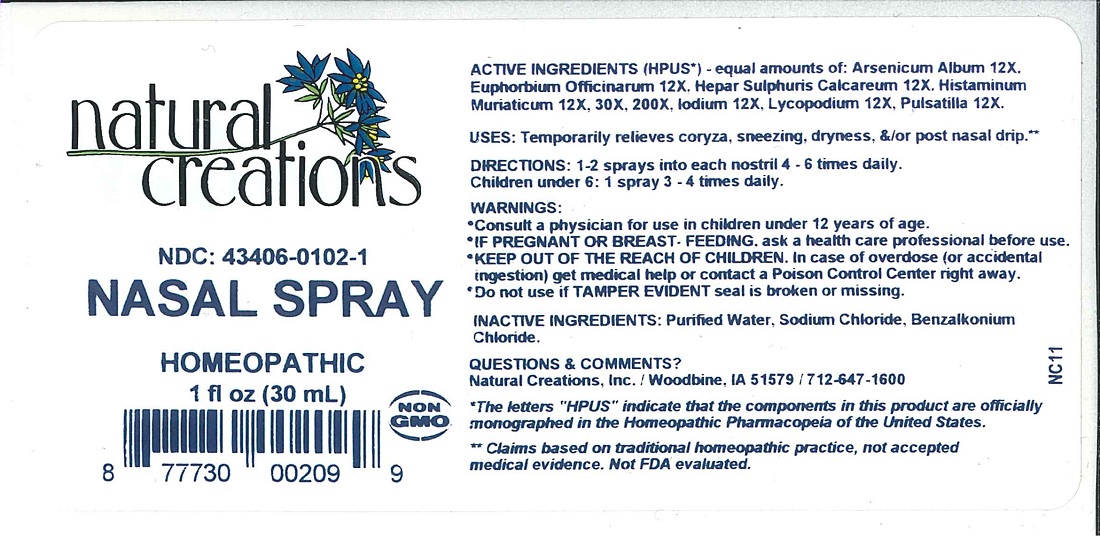 DRUG LABEL: Nasal
NDC: 43406-0102 | Form: LIQUID
Manufacturer: Natural Creations, Inc
Category: homeopathic | Type: HUMAN OTC DRUG LABEL
Date: 20251216

ACTIVE INGREDIENTS: ARSENIC TRIOXIDE 12 [hp_X]/1 mL; EUPHORBIA RESINIFERA RESIN 12 [hp_X]/1 mL; CALCIUM SULFIDE 12 [hp_X]/1 mL; HISTAMINE DIHYDROCHLORIDE 12 [hp_X]/1 mL; IODINE 12 [hp_X]/1 mL; LYCOPODIUM CLAVATUM SPORE 12 [hp_X]/1 mL; ANEMONE PULSATILLA 12 [hp_X]/1 mL
INACTIVE INGREDIENTS: water; SODIUM CHLORIDE; BENZALKONIUM CHLORIDE

NASAL SPRAY

ACTIVE INGREDIENT

ACTIVE INGREDIENTS (*HPUS) - equal amounts of: Arsenicum Album 12X, Euphorbium Officinarum 12X, Hepar Sulphuris Calcareum 12X, Histaminum 12X, 30X, 200X, Iodium 12X, Lycopodium 12C, Pulsatilla 12X.

INDICATIONS AND USAGE

USES: Temporarily relieves coryza, sneezing, dryness, &/or post nasal drip.**

PURPOSE

USES: Temporarily relieves coryza, sneezing, dryness, &/or post nasal drip.**

DOSAGE AND ADMINISTRATION

DIRECTIONS: 1-2 sprays into each nostril 4-6 times daily. Children under 6: 1 spray 3-4 times daily.

KEEP OUT OF REACH OF CHILDREN

KEEP OUT OF THE REACH OF CHILDREN. In case of overdose (or accidental ingestion) get medical help or contact a Poison Control Center right away.

WARNINGS:

- Consult a physician for use in children under 12 years of age.
- IF PREGNANT OR BREAST-FEEDING, ask a health care professional before use.
- KEEP OUT OF THE REACH OF CHILDREN. In case of overdose (or accidental ingestion) get medical help or contact a Poison Control Center right away.
- Do not use if TAMPER EVIDENT seal is broken or missing.

INACTIVE INGREDIENT

INACTIVE INGREDIENTS: Purified Water, Sodium Chloride, Benzalkonium Chloride.

QUESTIONS & COMMENTS?

Natural Creations, Inc. / Woodbine, IA 51579 / 712-647-1600

REFERENCES

*The letters "HPUS" indicate the components in this product are officially monographed in the Homeopathic Pharmacopeia of the United States.

**Claims based on traditional homeopathic practice, not accepted medical evidence. Not FDA evaluated.

PACKAGE LABEL

NDC: 43406-0102-1

NASAL SPRAY

HOMEOPATHIC

1 fl oz (30 mL)